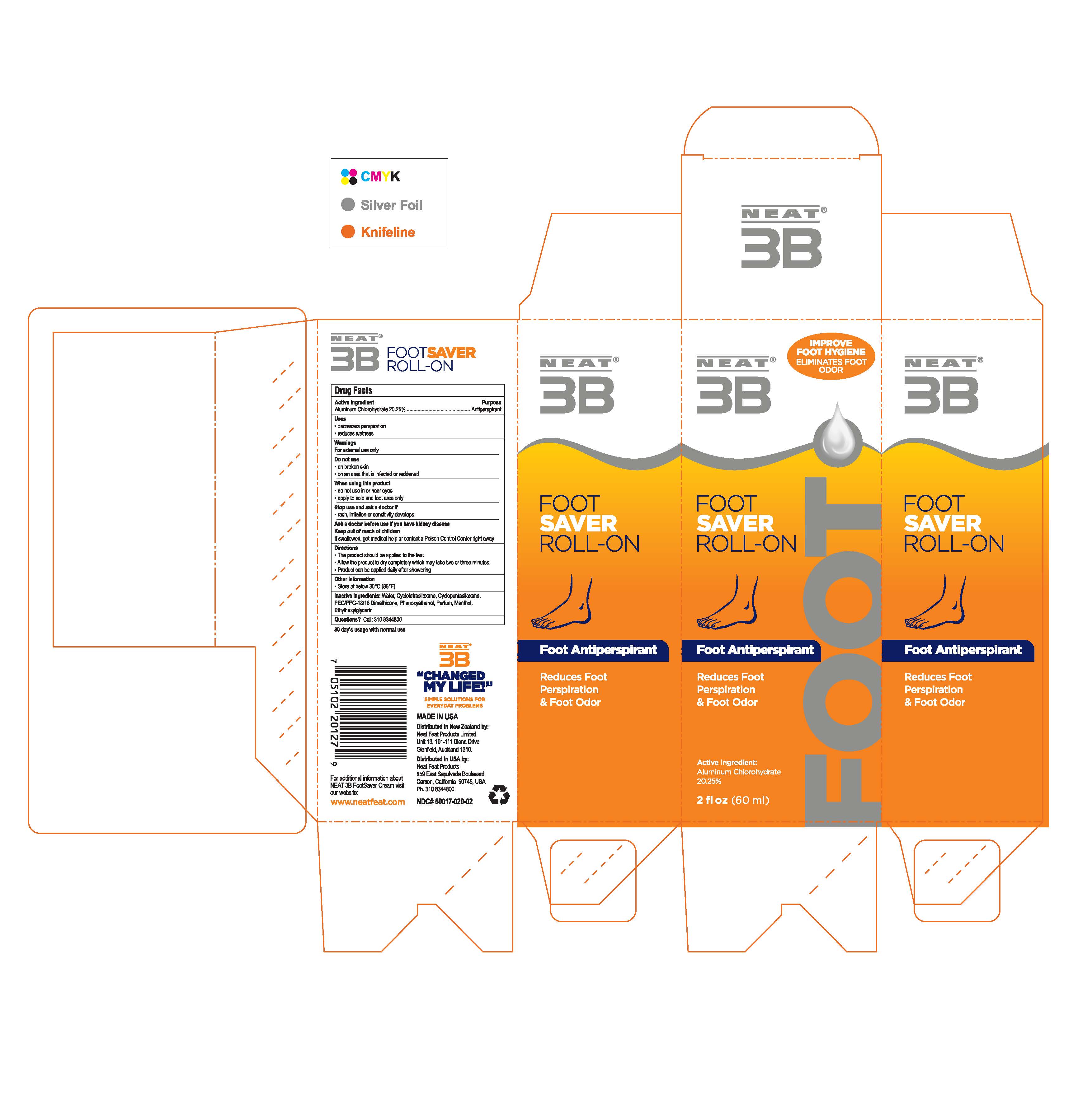 DRUG LABEL: Foot Saver
NDC: 50017-020 | Form: GEL
Manufacturer: Neat Feat Products Limited
Category: otc | Type: HUMAN OTC DRUG LABEL
Date: 20231101

ACTIVE INGREDIENTS: ALUMINUM CHLOROHYDRATE 13.5 g/60 mL
INACTIVE INGREDIENTS: ETHYLHEXYLGLYCERIN; MENTHOL, UNSPECIFIED FORM; CYCLOMETHICONE 4; WATER; PEG/PPG-18/18 DIMETHICONE; CYCLOMETHICONE 5; METHYLPARABEN; PHENOXYETHANOL

NEAT® 3B FOOT SAVER ROLL-ON

Drug Facts

Active Ingredient

Aluminum Chlorohydrate 20.25%

Purpose

Antiperspirant

Uses

- decreases perspiration
- reduces wetness

Warnings

For external use only

Do not use

- on broken skin
- on an area that is infected or reddened

When using this product

- do not use in or near eyes
- apply to sole and foot area only

Stop use and ask a doctor if

- rash, irritation or sensitivity develops

Ask a doctor before use if you have kidney disease

Keep out of reach of children

If swallowed, get medical help or contact a Poison Control Center right away

Directions

- The product should be applied to the feet
- Allow the product to dry completely which may take two or three minutes.
- Product can be applied daily after showering

Other information

- Store at below 30°C (86°F)

Inactive Ingredients

Water, Cyclotetrasiloxane & Cyclopentasiloxane, PEG/PPG-18/18 Dimethicone, Methylparaben, Phenoxyethanol, Ethylhexylglycerin, Fragrance, Menthol.

Questions?

Call: 310 8344800

MADE IN USA

Distributed in USA by:
Neat Feat Products

859 East Sepulveda Boulevard
Carson, California 90745, USA

Ph 310 8344800

Distributed in New Zealand by:
Neat Feat Products Limited
Unit 13, 101-111 Diana Drive

Glenfield, Auckland 1310.

Principal Display Panel - 60 ml Tube Box

NEAT®
3B

FOOT SAVER
ROLL-ON

Reduces Foot
Perspiration
& Foot Odor

Antiperspirant

Suitable for the Active
Work or Sports Person

Effective Extra Protection

www.neatfeat.com

Active Ingredient:
Aluminum Chlorohydrate
20.25%

2 fl oz (60ml)